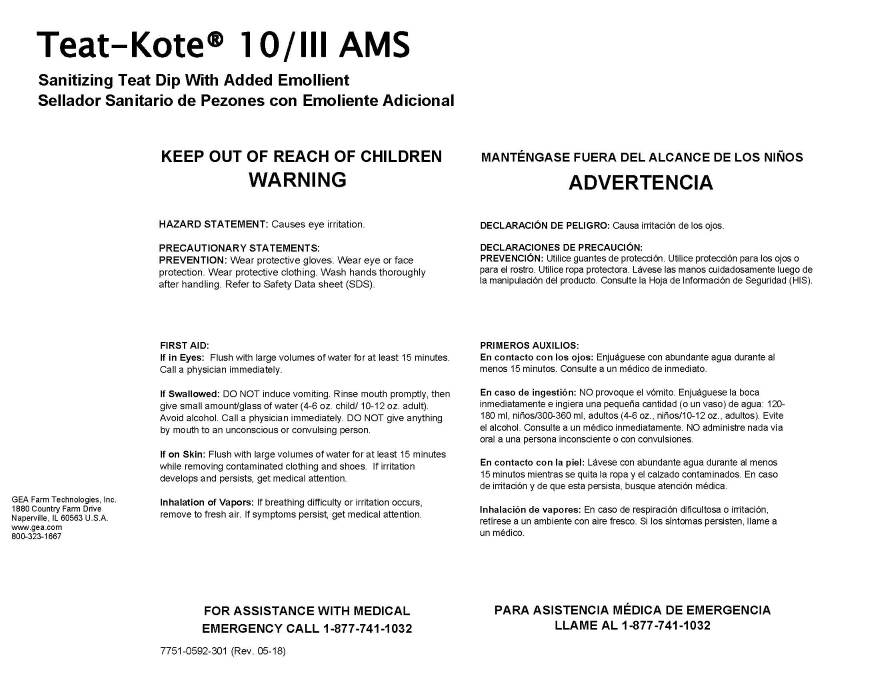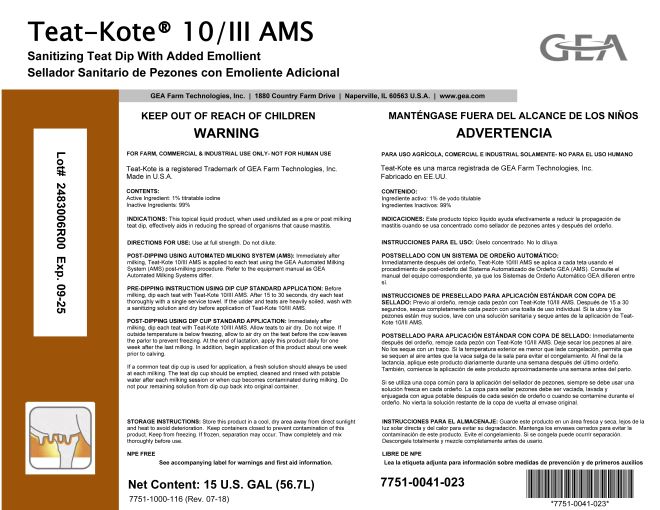 DRUG LABEL: Teat-Kote 10/III AMS
NDC: 51070-8010 | Form: LIQUID
Manufacturer: GEA Farm Technologies, Inc.
Category: animal | Type: OTC ANIMAL DRUG LABEL
Date: 20240904

ACTIVE INGREDIENTS: Iodine 1 g/100 g
INACTIVE INGREDIENTS: ALLANTOIN; ALOE VERA LEAF; PROPYLENE GLYCOL; XANTHAN GUM; POLOXAMER 335; GLYCERIN; PEG-75 LANOLIN; POTASSIUM IODIDE; POVIDONE K30; CITRIC ACID MONOHYDRATE

Teat-Kote 10/III AMS

ACTIVE INGREDIENT

CONTENTS:

Active Ingredient: 1% titratable iodine

Inactive Ingredients: 99%

Net Content: 15 U.S. GAL (56.7L)

KEEP OUT OF REACH OF CHILDREN

WARNING

PRECAUTIONS

HAZARD STATEMENT: Causes eye irritation.

PRECAUTIONARY STATEMENTS:

PREVENTION: Wear protective gloves. Wear eye or face protection. Wear protective clothing. Wash hands thoroughly after handling. Refer to Safety Data sheet (SDS).

USER SAFETY WARNINGS

FIRST AID:

If in Eyes: Flush with large volumes of water for at least 15 minutes. Call a physician immediately.
If Swallowed: DO NOT induce vomiting. Rinse mouth promptly, then give small amount/glass of water (4-6 oz. child / 10-12 oz. adult). Avoid alcohol. Call a physician immediately. DO NOT give anything by mouth to an unconscious or convulsing person.
If on Skin: Flush with large volumes of water for at least 15 minutes while removing contaminated clothing and shoes. If irritation develops and persists, get medical attention.
Inhalation of Vapors: If breathing difficulty or irritation occurs, remove to fresh air. If symptoms persist, get medical attention.

FOR ASSISTANCE WITH MEDICAL EMERGENCY

CALL 1-877-741-1032

FOR FARM, COMMERCIAL & INDUSTRIAL USE ONLY- NOT FOR HUMAN USE

Teat-Kote is a Trademark of GEA Farm Technologies, Inc.

Made in U.S.A.

INDICATIONS AND USAGE

INDICATIONS: This topical liquid product, when used undiluted as a pre or post milking teat dip, effectively aids in reducing the spread of organisms that cause mastitis.

DOSAGE AND ADMINISTRATION

DIRECTIONS FOR USE: Use at full strength. Do not dilute.

POST-DIPPING USING AUTOMATED MILKING SYSTEM (AMS): Immediately after milking, Teat-Kote 10/III AMS is applied to each teat using GEA Automated Milking System (AMS) post-milking procedure. Refer to the equipment manual as GEA Automated Milking Systems differ.

PRE-DIPPING INSTRUCTION USING DIP CUP STANDARD APPLICATION: Before milking, dip each teat with Teat-Kote 10/III AMS. After 15 to 30 seconds, dry each treat thoroughly with a single service towel. If the udder and teats are heavily soiled, wash with a sanitizing solution and dry before application of Teat-Kote 10/III AMS.

POST-DIPPINGUSING DIP CUP STANDARD APPLICATION: Immediately after milking, dip each teat with Teat-Kote 10/III AMS. Allow teats to air dry. Do not wipe. If outside temperature is below freezing, allow to air dry on the teat before the cow leaves the parlor to prevent freezing. At the end of lactation, apply this product daily for one week after the last milking. In addition, begin application of this product about one week prior to calving.

If a common teat dip cup is used for application, a fresh solution should always be used at each milking. The teat dip cup should be emptied, cleaned and rinsed with potable waterafter each milking session or when cup becomes contaminated during milking. Do not pour remaining solutionfrom dip cup back into original container.

STORAGE INSTRUCTIONS:

Store this product in a cool, dry area away from direct sunlight and heat to avoid deterioration. Keep containers closed to prevent contamination of this product. Keep from freezing. If frozen separation may occur. Thaw completely and mix thoroughly before use.

NPE FREE

See accompanying label for warnings and first aid information.

7751-1000-116 (Rev. 07-18)

GEA Farm Technologies, Inc. • 1880 Country Farm Drive • Naperville, IL 60563 U.S.A • www.gea.com

7751-0041-023

GEA Farm Technologies, Inc.

1880 Country Farm Dr.

Naperville, IL 60563 U.S.A.

www.gea.com

800-323-1667

7751-0592-301 (Rev. 05-18)

PACKAGE LABEL

Teat-Kote® 10/III AMS

Sanitizing Teat Dip With Added Emollient